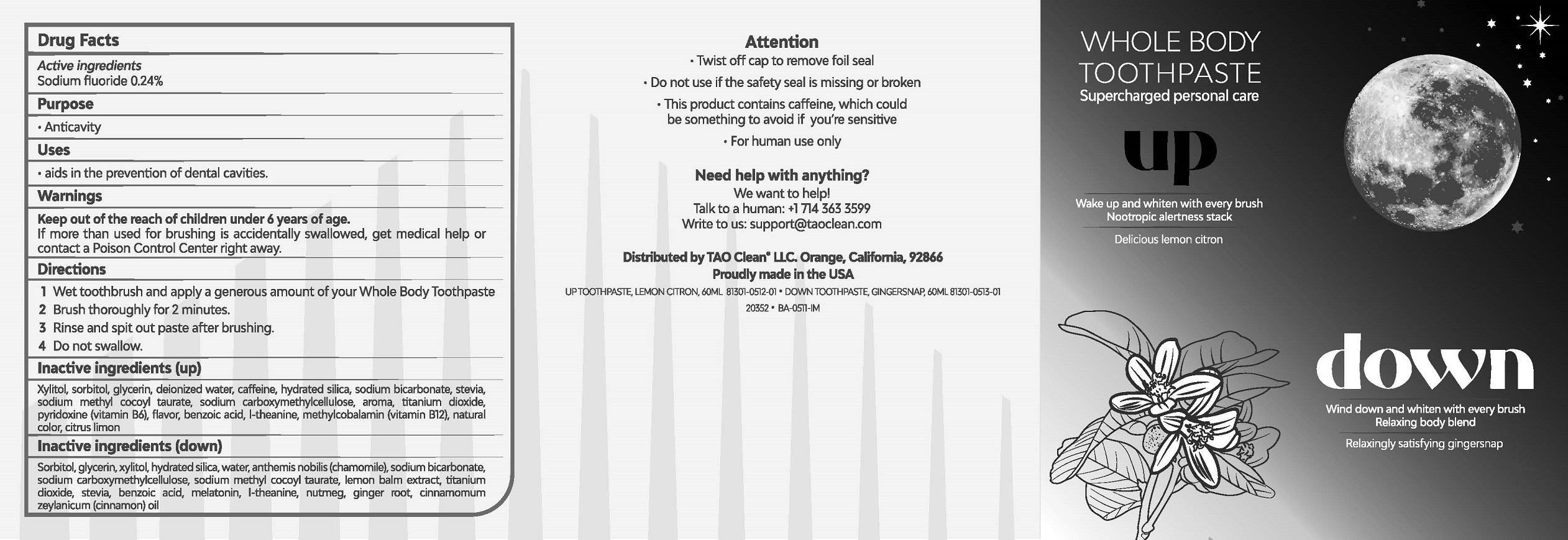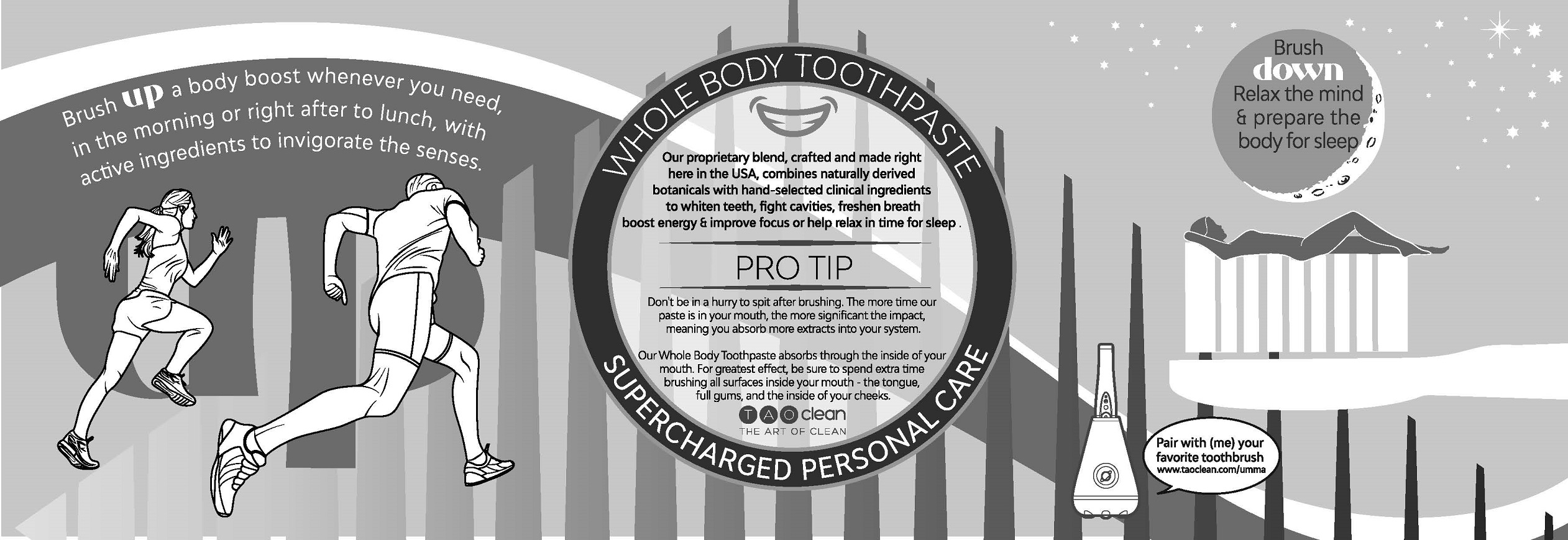 DRUG LABEL: UP Toothpaste,Lemon Citron
NDC: 81301-0512 | Form: PASTE, DENTIFRICE
Manufacturer: TAO CLEAN, LLC
Category: otc | Type: HUMAN OTC DRUG LABEL
Date: 20221021

ACTIVE INGREDIENTS: SODIUM FLUORIDE 1.1 mg/1 g
INACTIVE INGREDIENTS: STEVIA LEAF; SODIUM METHYL COCOYL TAURATE; PYRIDOXINE; BENZOIC ACID; THEANINE; WATER; HYDRATED SILICA; SODIUM BICARBONATE; CARBOXYMETHYLCELLULOSE SODIUM; TITANIUM DIOXIDE; XYLITOL; SORBITOL; GLYCERIN; CAFFEINE; METHYLCOBALAMIN

Active ingredients

Sodium fluoride 0.24%

Purpose

Anticavity

Uses

aids in the prevention of dental cavities.

Warnings

If more than used for brushing is accidentally swallowed, get medical help or

contact a Poison Control Center right away.

KEEP OUT OF REACH OF CHILDREN

Keep out of the reach of children under 6 years of age.

Directions

1 Wet toothbrush and apply a generous amount of your Whole Body Toothpaste

2 Brush thoroughly for 2 minutes.

3 Rinse and spit out paste after brushing.

4 Do not swallow.

Inactive ingredients

Inactive ingredients (up): Sorbitol, glycerin, xylitol, water, hydrated silica, chamomile, sodium carboxymethylcellulose, sodium methyl cocoyl taurate, sodium bicarbonate, lemon balm, titanium dioxide, stevia, sodium fluoride, benzoic acid, melatonin, L-Theanine

Inactive ingredients (down): sorbitol, glycerin, xylitol, hydrated silica, water, anthemis nobilis (chamomile), sodium bicarbonate, sodium carboxymethylcellulose, sodium methyl cocoyl taurate, lemon balm extract, titanium dioxide, stevia, benzoic acid, melatonin, l-theanine, nutmeg, ginger root, cinnamomum zeylanicum (cinnamon) oil

Attention

Twist off cap to remove foil seal

Do not use if the safety seal is missing or broken

This product contains caffeine, which could be something to avoid if you are sensitive

For human use only

Need help with anything?

We want to help!

Talk to a human: +1 714 363 3599

Write to us: support@taoclean.com

Distributed by TAO Clean® LLC. Orange, CA 92866

Proudly made in the USA

UP TOOTHPASTE, LEMON CITRON, 60 ML 81301-0512-01 • DOWN TOOTHPASTE, GINGERSNAP, 60 ML 81301-0513-01

20352 • BA-0511-IM